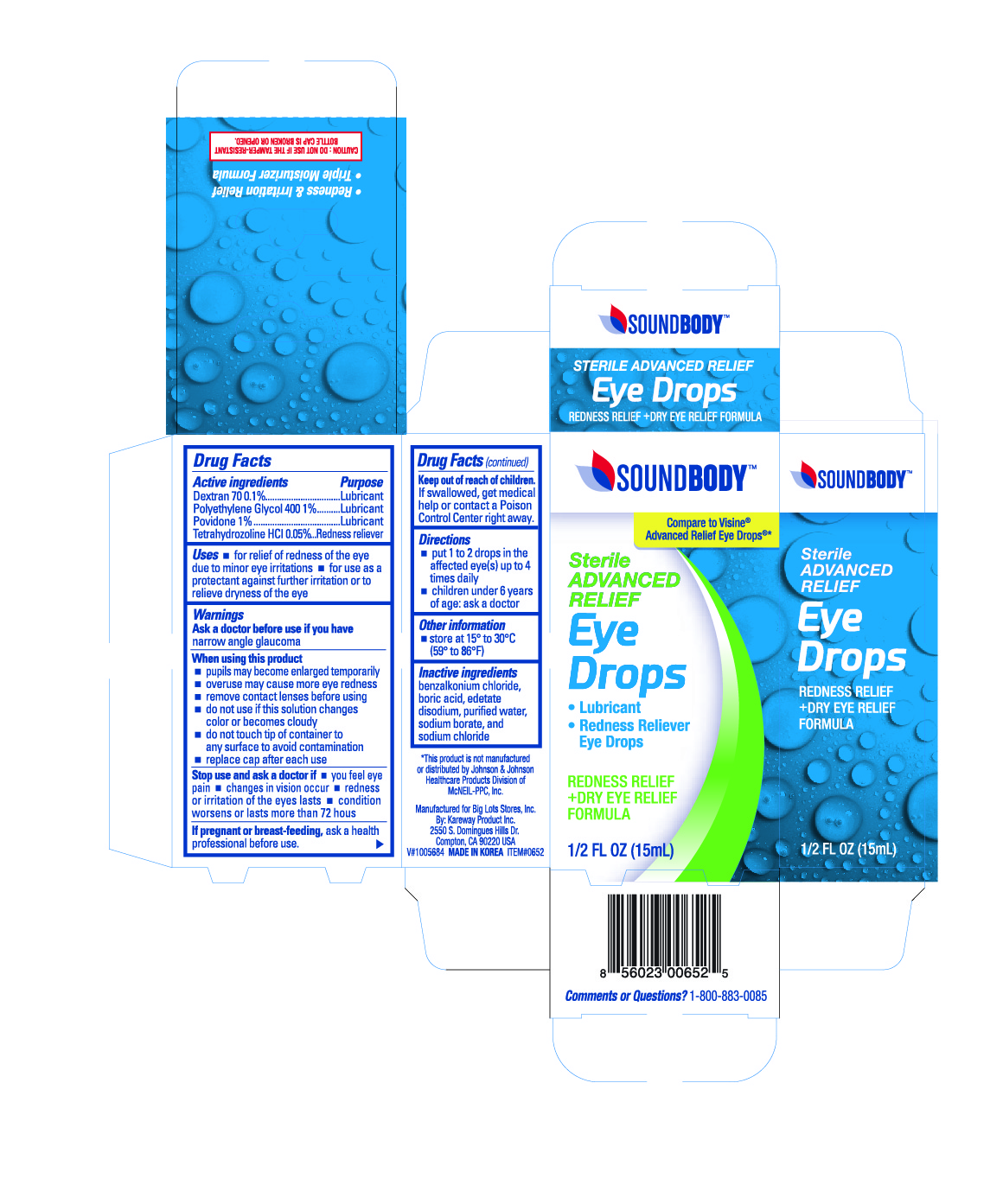 DRUG LABEL: Soundbody Advanced relief
NDC: 67510-0652 | Form: LIQUID
Manufacturer: Kareway Product, Inc.
Category: otc | Type: HUMAN OTC DRUG LABEL
Date: 20220708

ACTIVE INGREDIENTS: TETRAHYDROZOLINE HYDROCHLORIDE 0.5 mg/1 mL; DEXTRAN 70 1 mg/1 mL; POLYETHYLENE GLYCOL 400 10 mg/1 mL; POVIDONE 10 mg/1 mL
INACTIVE INGREDIENTS: BORIC ACID; SODIUM BORATE; EDETATE DISODIUM; BENZALKONIUM CHLORIDE; SODIUM CHLORIDE; WATER

Soundbody Advanced Relief Eye Drops

Active Ingredient

Dextran 70 0.1%

Polyethylene Glycol 400 1%

Povidone 1%

Tetrahydrozoline HCl 0.5%

Purpose

Lubricant

Lubricant

Lubricant

Redness reliever

Use

- for the relief of redness of the eye due to minor eye irritations
- for use as a protectant against further irritation or to relieve dryness of the eye

Warnings

Ask a doctor before use if you have narrow angle glaucoma

When using this product

- pupils may become enlarged temporarily
- overuse may cause more eye redness
- remove contact lenses before using
- do not use if this solution changes color or become cloudy
- do not touch tip of container to any surface to avoid contamination
- replace cap after each use

Stop use and ask a doctor if

- you feel eye pain
- changes in vision occur
- redness or irritation of the eye lasts
- condition worsens or lasts more than 72 hours

If pregnant or breast-feeding,

ask a health professional before use.

Keep out of reach of children.

If swallowed, get medical help or contact a Poison Control Center right away.

Directions

- Put 1 to 2 drops in the affected eye(s) up to 4 times daily
- children under 6 years of age: ask a doctor

Other information

- store between 15° to 25°C (59°F to 77°F)

Inactive ingredients

boric acid, sodium borate, edetate disodium, benzalkonium chloride, sodium chloride, dilite hydrochloric acid, sterile purified water

package label

Soundbody Advance relief Eye Drops